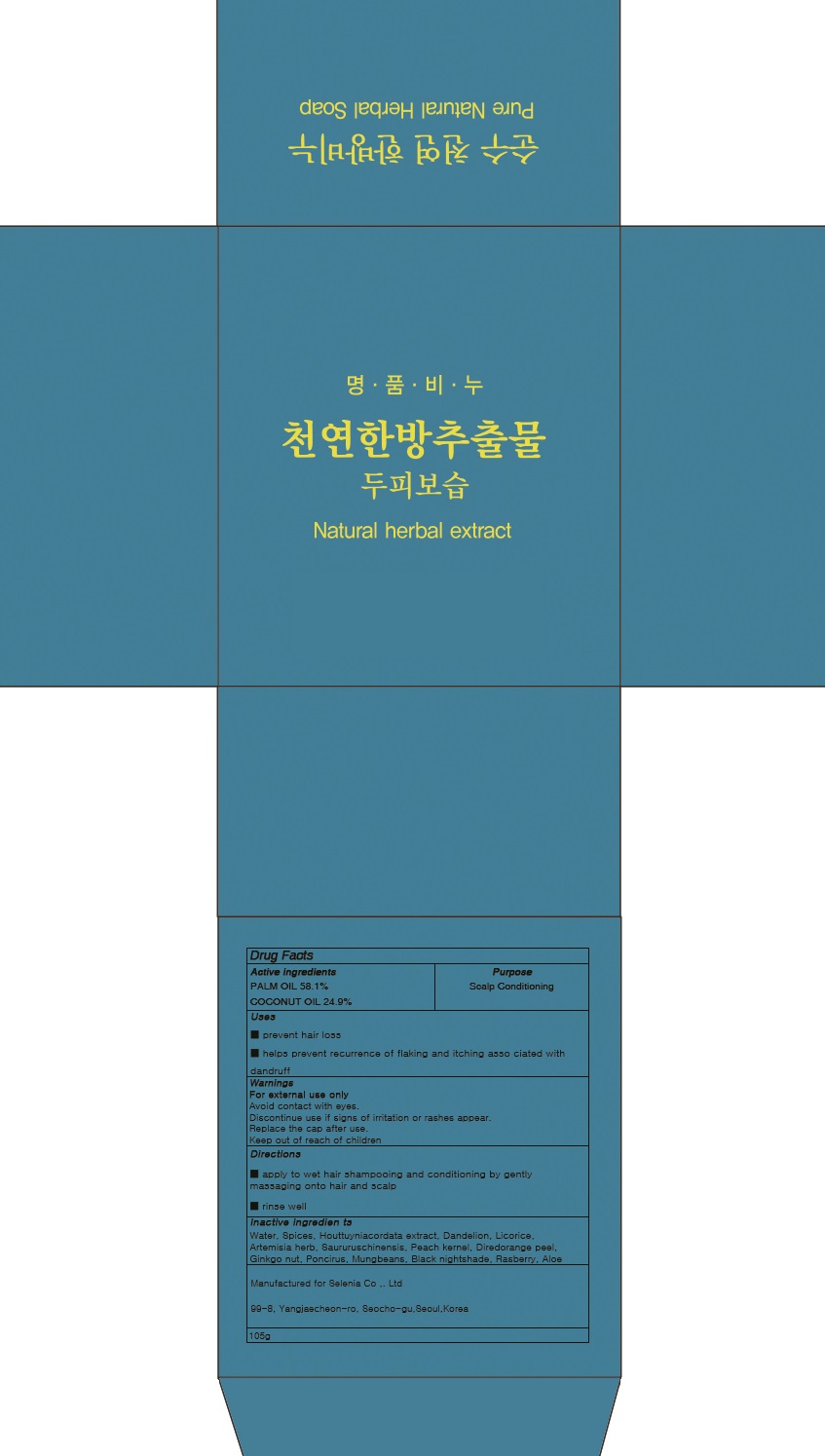 DRUG LABEL: Hair Loss and Scalp Moisturizing
NDC: 71946-010 | Form: SOAP
Manufacturer: Selenia
Category: otc | Type: HUMAN OTC DRUG LABEL
Date: 20180103

ACTIVE INGREDIENTS: PALM OIL 61.0 g/105 g; COCONUT OIL 24.9 g/105 g
INACTIVE INGREDIENTS: Water

ACTIVE INGREDIENT

Active ingredients: PALM OIL 58.1%, COCONUT OIL 24.9%

INACTIVE INGREDIENT

Inactive ingredients: Water, Spices, Houttuyniacordata extract, Dandelion, Licorice, Artemisia herb, Saururuschinensis, Peach kernel, Dried orange peel, Ginkgo nut, Poncirus, Mungbeans, Black nightshade, Rasberry, Aloe

PURPOSE

Purpose: Scalp Conditioning

WARNINGS

Warnings: For external use only Avoid contact with eyes. Discontinue use if signs of irritation or rashes appear. Replace the cap after use. Keep out of reach of children

KEEP OUT OF REACH OF CHILDREN

Uses

- prevent hair loss

- helps prevent recurrence of flaking and itching associated with dandruff

Directions

1) apply to wet hair shampooing and conditioning by gently massaging onto hair and scalp

2) rinse well